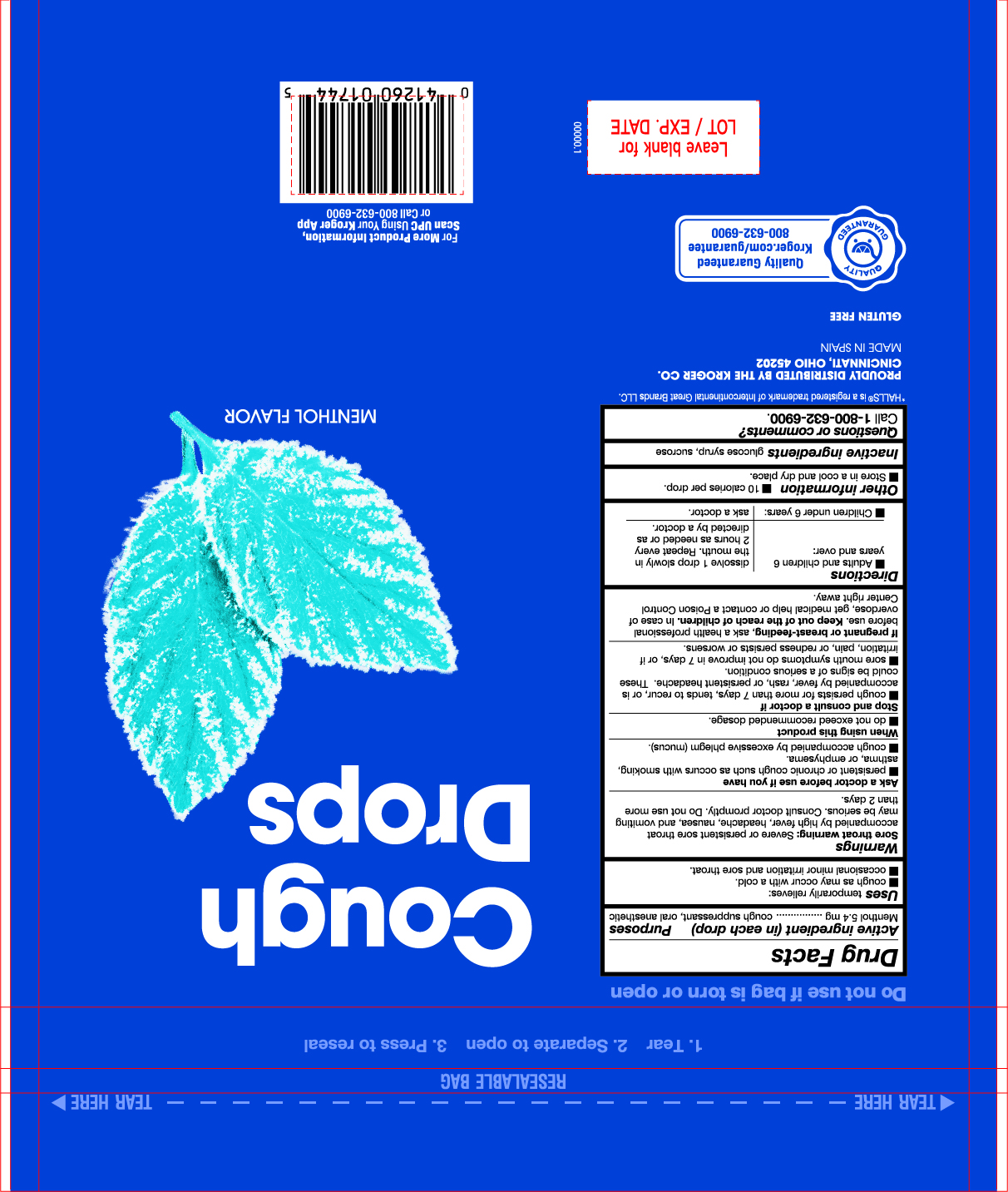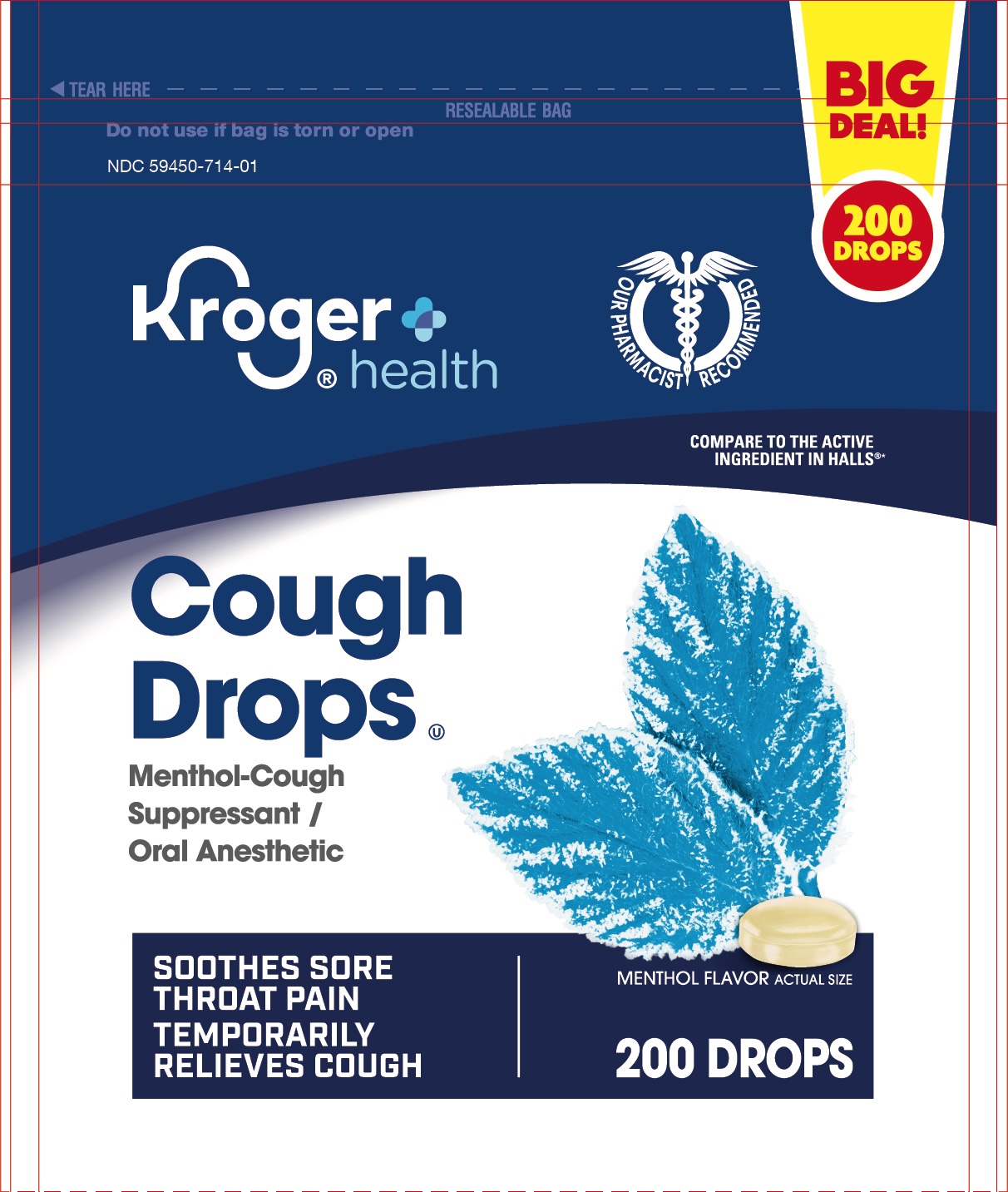 DRUG LABEL: Cough Drops
NDC: 59450-714 | Form: PASTILLE
Manufacturer: The Kroger CO
Category: otc | Type: HUMAN OTC DRUG LABEL
Date: 20250209

ACTIVE INGREDIENTS: MENTHOL 5.4 mg/1 1
INACTIVE INGREDIENTS: SUCROSE; CORN SYRUP

Cough Drops

Active ingredient 5.4 mg

Cough Suppressant

Oral anesthetic

PURPOSE

Uses temporarily relieves:

- cough as may occur with a cold
- ocassional minor irritation and sore throat

INDICATIONS AND USAGE

Uses temporarily relieves:

- cough as may occur with a cold
- ocassional minor irritation and sore throat

Warnings

Sore throat warning: severe or persistence sore throat accompanied by high fever, headache, nausea and vomiting may be serious. Consult a doctor promptly. Do not use more than 2 days or administer to children under 12 years of age.

Ask a doctor before use if you have

- a severe throat accompanied by difficulty in breathing or that last more than 2 days
- a sore throat accompanied by fever, headache, rash, swelling, nausea or vomiting

Stop use and consult a doctor if

- sore mouth symptons do not improve in 7 days or if irritation, pains or redness persists or worsens.

PREGNANCY OR BREAST FEEDING

If pregnant or breast-feeding, ask a health professional before use.

KEEP OUT OF REACH OF CHILDREN

Keep this and all drugs out of the reach of children.

OVERDOSAGE

In case of accidental overdose, get medical help or contact a Poison Control Center right away.

Directions

- Adults and children 12 years and over: dissolve 1 drop slowly in mouth. Repeated every 2 hours as needed or as directed by a doctor.
- Children under 12 years and under do not use

OTHER SAFETY INFORMATION

- Store in a cool and dry place
- 10 calories per drop

INACTIVE INGREDIENT

glucose syrup, sucrose

Questions or comments: 1-800-632-6900